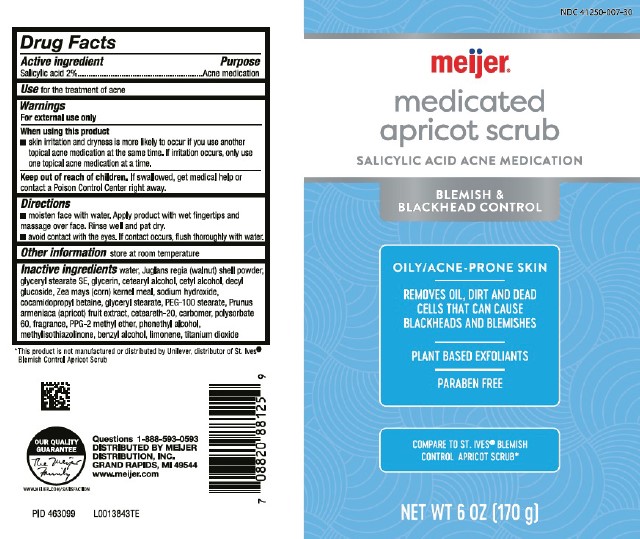 DRUG LABEL: Medicated Apricot Scrub
NDC: 41250-007 | Form: GEL
Manufacturer: Meijer, Inc.
Category: otc | Type: HUMAN OTC DRUG LABEL
Date: 20260219

ACTIVE INGREDIENTS: SALICYLIC ACID 20 mg/1 g
INACTIVE INGREDIENTS: WATER; JUGLANS REGIA SHELL; GLYCERYL STEARATE SE; GLYCERIN; CETOSTEARYL ALCOHOL; CETYL ALCOHOL; DECYL GLUCOSIDE; CORN GRAIN; SODIUM HYDROXIDE; COCAMIDOPROPYL BETAINE; GLYCERYL MONOSTEARATE; PEG-100 STEARATE; APRICOT; POLYOXYL 20 CETOSTEARYL ETHER; CARBOMER HOMOPOLYMER, UNSPECIFIED TYPE; POLYSORBATE 60; PPG-2 METHYL ETHER; PHENYLETHYL ALCOHOL; METHYLISOTHIAZOLINONE; BENZYL ALCOHOL; LIMONENE, (+)-; TITANIUM DIOXIDE

Meijer 041.006/041AK
Medicated Apricot Scrub

Active ingredient

Salicylic acid 2%

Purpose

Acne medication

Use

for the treatment of acne

Warnings

For external use only

When using this product

skin irritation and dryness is more likely to occur if you use another topical acne medication at the same time. If irritation occurs, only use one topical acne medication at a time.

Keep out of reach of children.

If swallowed, get medical help or contact a Poison Control Center right away.

Directions

- moisten face with water. Apply product with wet fingertips and massage over face. Rinse well and pat dry.
- avoid contact with the eyes. If contact occurs, flush thoroughly with water.

Other information

Store at room temperature

Inactive ingredients

water, Juglans regia (walnut) shell powder, glyceryl stearate SE, glycerin, cetearyl alcohol, cetyl alcohol, decyl glucoside, Zea mays (corn) kernel meal, sodium hydroxide, cocamidopropyl betaine, glyceryl stearate, PEG-100 stearate, Prunus armeniaca (apricot) fruit extract, ceteareth-20, carbomer, polysorbate 60, fragrance, PPG-2 methyl ether, phenethyl alcohol, methylisothiazolinone, benzyl alcohol, limonene, titanium dioxide

Disclaimer

*This product is not manufactured or distributed by Unilever, distributor of St. Ives®Blemish Control Apricot Scrub.

Adverse Reaction

OUR QUAILITY GUARANTEE

The Meijer Family

WWW.MEIJER.COM/SATISFACTION

Questions 1-888-593-0593

DISTRIBUTED BY MEIJER DISTRIBUTION, INC.
GRAND RAPIDS, MI 49544
www.meijer.com

principal display panel

NDC 41250-007-30

Meijer®

medicated apricot scrub

SALICYLIC ACID ACNE MEDICATION

BLEMISH & BREAKOUT CONTROL

OILY/ACNE-PRONE SKIN

REMOVES OIL, DIRT AND DEAD CELLS THAT CAN CAUSE BLACKHEADS AND BLEMISHES

PLANT BASED EXFOLIANTS

PARABEN FREE

COMPARE TO ST. IVES®BLEMISH CONTROL APRICOT SCRUB*

NET WT 6 OZ (170 g)